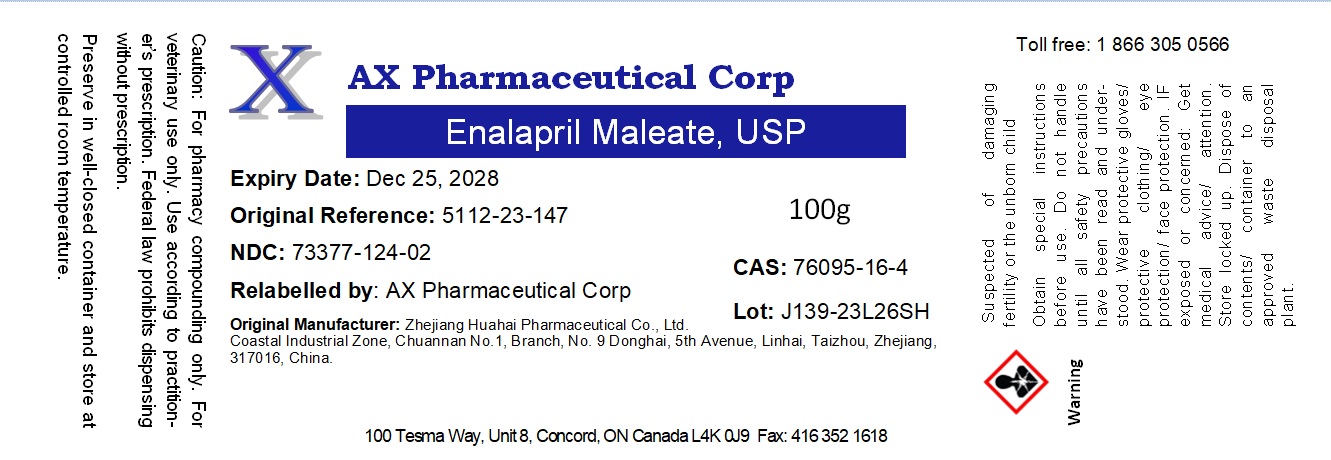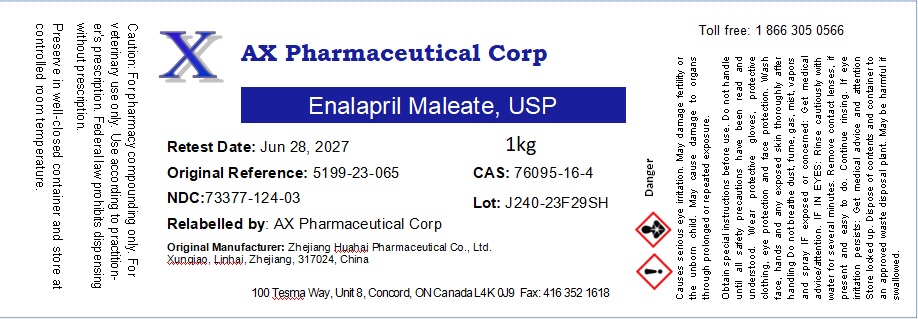 DRUG LABEL: Enalapril Maleate
NDC: 73377-124 | Form: POWDER
Manufacturer: AX Pharmaceutical Corp
Category: other | Type: BULK INGREDIENT - ANIMAL DRUG
Date: 20260119

ACTIVE INGREDIENTS: ENALAPRIL MALEATE 1 g/1 g

Enalapril Maleate